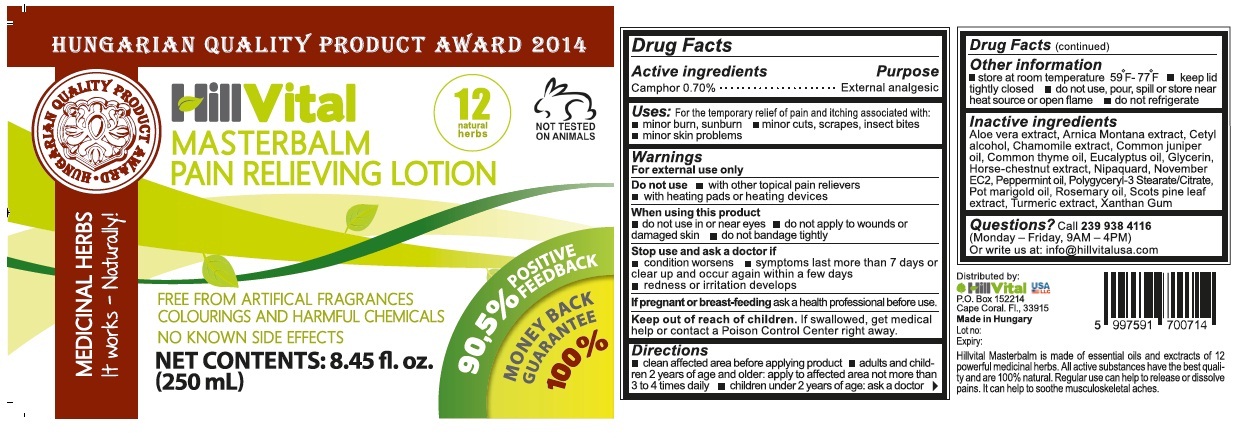 DRUG LABEL: Masterbalm
NDC: 70823-101 | Form: LOTION
Manufacturer: Biomaster-agro Kereskedelmi Es Szolgaltato Korlatolt Felelossegu Tarsasag
Category: otc | Type: HUMAN OTC DRUG LABEL
Date: 20160915

ACTIVE INGREDIENTS: CAMPHOR (NATURAL) 0.7 g/100 mL
INACTIVE INGREDIENTS: ALOE VERA LEAF; ARNICA MONTANA; CETYL ALCOHOL; CHAMOMILE; JUNIPERUS OXYCEDRUS LEAF OIL; THYME OIL; EUCALYPTUS OIL; GLYCERIN; HORSE CHESTNUT; SORBITAN; PROPANEDIOL; BENZOIC ACID; SODIUM ACRYLATE; BEHENETH-25; BEHENETH-25 METHACRYLATE; HYDROGENATED POLYDECENE (550 MW); LAURYL GLUCOSIDE; PEPPERMINT OIL; POLYGLYCERYL-3 DISTEARATE; CALENDULA OFFICINALIS SEED OIL; ROSEMARY OIL; PINUS SYLVESTRIS SPROUT; TURMERIC; XANTHAN GUM

HillVital MASTERBALM PAIN RELIEVING LOTION

Active ingredients

Camphor 0.70%

Purpose

External analgesic

INDICATIONS AND USAGE

Uses: For the temporarily relief of pain and itching associated with:

• minor burn, sunburn • minor cuts, scrapes, insect bites

• minor skin problems.

Warnings

For external use only.

Do not use • with other topical pain relievers • with heating pads or heating devices.

When using this product

• do not use in or near eyes • do not apply to wounds or damaged skin • do not bandage tightly

Stop use and ask a doctor if

• condition worsens • symptoms last more than 7 days or clear up and occur again within a few days • redness or irritation develops

If pregnant or breast-feeding ask a health professional before use.

Keep out of reach of children. If swallowed, get medical help or contact a Poison Control Centre right away.

Directions

• clean affected area before applying product • adults and children 2 years of age and older: apply to affected area not more than 3 to 4 times daily. • children under 2 years of age: ask a doctor

Inactive ingredients

Aloe vera extract, Arnica Montana extract, Cetyl alcohol, Chamomile extract, Common juniper oil, Common thyme oil, Eucalyptus oil, Glycerin, Horse-chestnut extract, Nipaquard, November EC2, Peppermint oil, Polyglyceryl-3 Stearate/Citrate, Pot marigold oil, Rosemary oil, Scots pine leaf extract, Turmeric extract, Xanthan Gum

Other information

• store at room temperature 59°F-77ºF • keep lid tightly close • do not use, pour, spill or store near heat source or open flame • do not refrigerate

Questions? Call 239 938 4116
(Monday- Friday, 9 AM- 4PM)
Or write us at: info@hillvitalusa.com

Distributed by:

HILLVITAL USA

P.O. Box 152214

Cape Coral, FL., 33915

Made in Hungary

Hillvital Masterbalm is made of essential oils and extracts of 12 powerful medicinal herbs. All active substances have the best quality and are 100% natural. Regular use can help to release or dissolve pains. It can help to soothe musculoskeletal aches.

FREE FROM ARTIFICIAL FRAGRANCES

COLOURINGS AND HARMFUL CHEMICALS

NO KNOWN SIDE EFFECTS

NOT TESTED ON ANIMALS

12 natural herbs

MEDICINAL HERBS